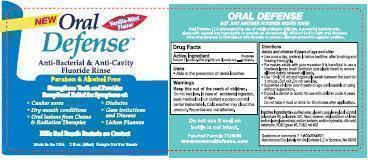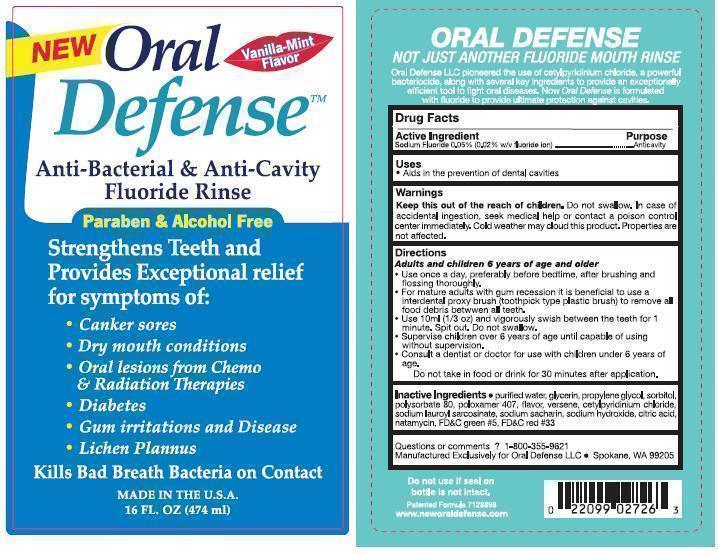 DRUG LABEL: Oral Defense Fluoride Rinse
NDC: 52644-002 | Form: MOUTHWASH
Manufacturer: Oral Defense, LLC
Category: otc | Type: HUMAN OTC DRUG LABEL
Date: 20130418

ACTIVE INGREDIENTS: SODIUM FLUORIDE .2418 g/474 mL
INACTIVE INGREDIENTS: WATER; EDETATE DISODIUM; POLOXAMER 407; PROPYLENE GLYCOL; CETYLPYRIDINIUM CHLORIDE; SORBITOL; SACCHARIN SODIUM ANHYDROUS; GLYCERIN; POLYSORBATE 80; NATAMYCIN; MINT; SODIUM LAUROYL SARCOSINATE; SODIUM HYDROXIDE; CITRIC ACID MONOHYDRATE

Oral Defense Fluoride Rinse

Drug Facts

Active Ingredients

Sodium Fluoride .05% (0.22% w/v fluoride ion)

Purpose

Anti-cavity

Uses

Aids in the prevention of dental cavities

Warnings

Do not swallow. In case of accidental ingestion, seek medical help or contact a poison control center immediately. Cold weather may cloud this product. Properties are not affected.

Directions

Adults and children 6 years of age and older

- Use once a day, preferably before bedtime, after brushing and flossing thoroughly.

- For mature adults with gum recession, it is beneficial to use an interdental proxy brush (toothpick type plastic brush) to remove all food debris between all teeth.

- Use 10ml (1/3oz) and vigorously swish between the teeth for 1 minute. Spit out. Do not swallow.

- Supervise children over 6 years of age until capable of suing without supervision.

- Consult with a dentist or doctor for use with children under 6 years of age.

- Do not take in food or drink for 30 minutes after application.

Inactive Ingredients

purified water, glycerin, propylene glycol, sorbitol, polysorbate 80, poloxamer 407, flavor, versene, cetylpyridinium chloride, sodium lauroyl sarcosinate, sodium saccharin, sodium hydroxide, citric acid, natamycin, FD and C green #5, FD and C red #33.